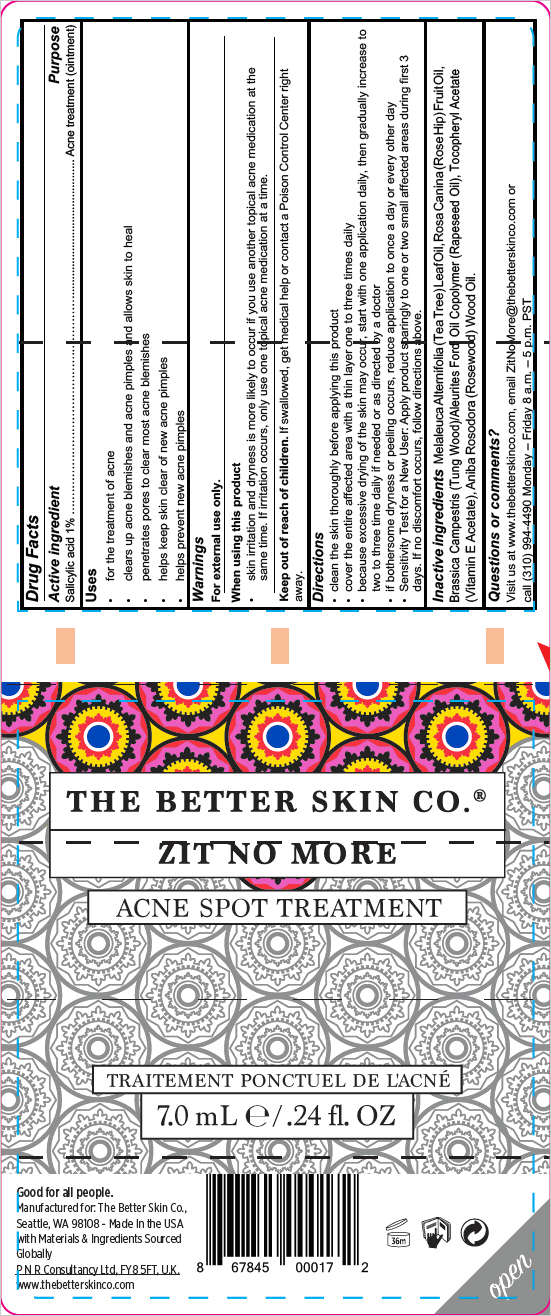 DRUG LABEL: THE BETTER SKIN CO. 
NDC: 71716-100 | Form: LIQUID
Manufacturer: Mirakle Cosmetics LLC dbaThe Better Skin Co.
Category: otc | Type: HUMAN OTC DRUG LABEL
Date: 20200626

ACTIVE INGREDIENTS: salicylic acid 10 mg/1 mL
INACTIVE INGREDIENTS: Tea Tree Oil; Rosa Canina Fruit Oil; .Alpha.-Tocopherol Acetate; ROSEWOOD OIL

THE BETTER SKIN CO.®
ZIT NO MORE

Drug Facts

Active ingredient

Salicylic acid 1%

Purpose

Acne treatment (ointment)

Uses

- for the treatment of acne
- clears up acne blemishes and acne pimples and allows skin to heal
- penetrates pores to clear most acne blemishes
- helps keep skin clear of new acne pimples
- helps prevent new acne pimples

Warnings

For external use only.

When using this product

- skin irritation and dryness is more likely to occur if you use another topical acne medication at the same time. If irritation occurs, only use one topical acne medication at a time.

Keep out of reach of children. If swallowed, get medical help or contact a Poison Control Center right away.

Directions

- clean the skin thoroughly before applying this product
- cover the entire affected area with a thin layer one to three times daily
- because excessive drying of the skin may occur, start with one application daily, then gradually increase to two to three time daily if needed or as directed by a doctor
- if bothersome dryness or peeling occurs, reduce application to once a day or every other day
- Sensitivity Test for a New User: Apply product sparingly to one or two small affected areas during first 3 days. If no discomfort occurs, follow directions above.

Inactive ingredients

Melaleuca Alternifolia (Tea Tree) Leaf Oil, Rosa Canina (Rose Hip) Fruit Oil, Brassica Campestris (Tung Wood)/Aleurites Fordi Oil Copolymer (Rapeseed Oil), Tocopheryl Acetate (Vitamin E Acetate), Aniba Rosodora (Rosewood) Wood Oil.

Questions or comments?

Visit us at www.thebetterskinco.com, email ZitNoMore@thebetterskinco.com or call (310) 994-4490 Monday – Friday 8 a.m. – 5 p.m. PST

PRINCIPAL DISPLAY PANEL - 7.0 mL Bag Label

THE BETTER SKIN CO.®
ZIT NO MORE

ACNE SPOT TREATMENT

7.0 mL e / .24 fl. OZ